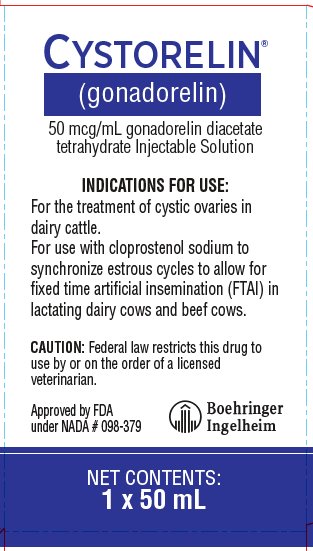 DRUG LABEL: CYSTORELIN
NDC: 0010-8283 | Form: INJECTION, SOLUTION
Manufacturer: Boehringer Ingelheim Animal Health USA Inc.
Category: animal | Type: PRESCRIPTION ANIMAL DRUG LABEL
Date: 20250805

ACTIVE INGREDIENTS: GONADORELIN DIACETATE TETRAHYDRATE 50 ug/1 mL
INACTIVE INGREDIENTS: BENZYL ALCOHOL 9 mg/1 mL; SODIUM CHLORIDE 7.47 mg/1 mL; WATER

CYSTORELIN®
(gonadorelin)
50 mcg/mL gonadorelin diacetate tetrahydrate Injectable Solution

For treatment of cystic ovaries in dairy cattle

For use with cloprostenol sodium to synchronize estrous cycles to allow for fixed time artificial insemination (FTAI) in lactating dairy cows and beef cows.

CAUTION:

Federal law restricts this drug to use by or on the order of a licensed veterinarian.

DESCRIPTION:

CYSTORELIN® is a sterile solution containing 43 mcg/mL of gonadorelin (GnRH) as 50 mcg/mL gonadorelin diacetate tetrahydrate suitable for intramuscular or intravenous administration according to the indication. Gonadorelin is a decapeptide composed of the sequence of amino acids—

5-oxoPro-His-Trp-Ser-Tyr-Gly-Leu-Arg-Pro-Gly-NH2—

a molecular weight of 1182.32 and empirical formula C55H75N17O13. The diacetate tetrahydrate ester has a molecular weight of 1374.48 and empirical formula C59H91N17O21.

Each mL of CYSTORELIN contains:

Gonadorelin diacetate tetrahydrate (equivalent to 43 mcg gonadorelin) 50 mcg

Benzyl Alcohol 9 mg

Sodium Chloride 7.47 mg

Water for Injection q.s.

pH adjusted with potassium phosphate (monobasic and dibasic).

Gonadorelin is the hypothalamic releasing factor responsible for the release of gonadotropins (e.g., luteinizing hormone [LH], follicle stimulating hormone [FSH]) from the anterior pituitary. Synthetic gonadorelin is physiologically and chemically identical to the endogenous bovine hypothalamic releasing factor.

INDICATIONS FOR USE:

Cystic Ovaries

CYSTORELIN is indicated for the treatment of ovarian follicular cysts in dairy cattle. Ovarian cysts are non-ovulated follicles with incomplete luteinization which result in nymphomania or irregular estrus. Historically, cystic ovaries have responded to an exogenous source of LH such as human chorionic gonadotropin. CYSTORELIN initiates release of endogenous LH to cause ovulation and luteinization.

Reproductive Synchrony

CYSTORELIN is indicated for use with cloprostenol sodium to synchronize estrous cycles to allow for fixed time artificial insemination (FTAI) in lactating dairy cows and beef cows.

DOSAGE AND ADMINISTRATION:

Cystic Ovaries

The intravenous or intramuscular dosage of CYSTORELIN is 100 mcg gonadorelin diacetate tetrahydrate (2 mL) per cow.

Reproductive Synchrony

The intramuscular dosage of CYSTORELIN is 100 mcg gonadorelin diacetate tetrahydrate (2 mL) per cow, used in reproductive synchrony programs similar to the following:

1. Administer the first CYSTORELIN injection (2 mL) at Time 0.

2. Administer 500 mcg cloprostenol (as cloprostenol sodium) by intramuscular injection 6 to 8 days after the first CYSTORELIN injection.

3. Administer the second CYSTORELIN injection (2 mL) 30 to 72 hours after the cloprostenol sodium injection.

4. Perform FTAI 0 to 24 hours after the second CYSTORELIN injection, or inseminate cows on detected estrus using standard herd practices.

WARNINGS AND PRECAUTIONS:

Not for use in humans.

Keep out of reach of children.

WITHDRAWAL PERIODS:

No withdrawal period or milk discard time is required when used according to the labeling.

To report suspected adverse drug events, for technical assistance or to obtain a copy of the Safety Data Sheet (SDS), contact Boehringer Ingelheim Animal Health USA Inc. at 1-888-637-4251. For additional information about adverse drug experience reporting for animal drugs, contact FDA at 1-888-FDA-VETS, or www.fda.gov/reportanimalae.

PHARMACOLOGY AND TOXICOLOGY:

Endogenous gonadorelin is synthesized and/or released from the hypothalamus during various stages of the bovine estrus cycle following appropriate neurogenic stimuli. It passes via the hypophyseal portal vessels, to the anterior pituitary to effect the release of gonadotropins (e.g., LH, FSH). Synthetic gonadorelin administered intravenously or intramuscularly also causes the release of endogenous LH or FSH from the anterior pituitary.

Gonadorelin diacetate tetrahydrate has been shown to be safe. The LD50 for mice and rats is greater than 60 mg/kg, and for dogs, greater than 600 mcg/kg, respectively. No adverse effects were noted among rats or dogs administered 120 mcg/kg/day or 72 mcg/kg/day intravenously for 15 days.

It had no adverse effects on heart rate, blood pressure, or EKG to unanesthetized dogs at 60 mcg/kg. In anesthetized dogs it did not produce depression of myocardial or system hemodynamics or adversely affect coronary oxygen supply or myocardial oxygen requirements.

The intravenous administration of 60 mcg/kg/day of gonadorelin diacetate tetrahydrate to pregnant rats and rabbits during organogenesis did not cause embryotoxic or teratogenic effects.

Further, CYSTORELIN did not cause irritation at the site of intramuscular administration in dogs with a dose of 72 mcg/kg/day administered for seven (7) days.

TARGET ANIMAL SAFETY:

In addition to the animal safety information presented in the PHARMACOLOGY AND TOXICOLOGY section, the safety of CYSTORELIN was established through the review and evaluation of the extensive published literature available for the use of gonadorelin-containing products.

The intramuscular administration of 1000 mcg gonadorelin diacetate tetrahydrate on five (5) consecutive days to normally cycling dairy cattle had no effect on hematology or clinical chemistries.

In field studies evaluating the effectiveness of CYSTORELIN for the treatment of ovarian follicular cysts, the incidence of health abnormalities was not significantly greater in cows administered CYSTORELIN than cows administered a placebo injection.

The target animal safety of, and injection site reactions to, gonadorelin when used with cloprostenol sodium were evaluated during the conduct of effectiveness field studies. The incidence of health abnormalities was not significantly greater in cows administered gonadorelin than cows administered a placebo injection.

EFFECTIVENESS:

The use of CYSTORELIN for treatment of ovarian follicular cysts in dairy cattle was demonstrated to be effective with a treatment dose of 100 mcg gonadorelin diacetate tetrahydrate.

The effectiveness of gonadorelin for use with cloprostenol sodium to synchronize estrous cycles to allow for FTAI in lactating dairy cows was demonstrated in a field study at 10 different locations in the U.S. Four of the locations represented conditions that would typically cause heat stress in lactating cows. A total of 1607 healthy, non-pregnant, primiparous or multiparous lactating dairy cows within 40-150 days postpartum were enrolled in the study. A total of 805 cows were administered gonadorelin (1 mL; 100 mcg gonadorelin as the acetate salt) and 802 cows were administered an equivalent volume of water for injection as an intramuscular injection twice in the following regimen:

Day 0: 100 mcg gonadorelin (as the acetate salt) or sterile water for injection

Day 7: 500 mcg cloprostenol (as cloprostenol sodium)

Day 9: 100 mcg gonadorelin (as the acetate salt) or sterile water for injection

Fixed time AI was performed on Day 10, approximately 11 - 31 hours after the Day 9 injection. Cows were evaluated for pregnancy on Day 45 ± 5 days by trans-rectal ultrasound or rectal palpation. Pregnancy rate to FTAI was significantly higher (P < 0.0001) in cows treated with gonadorelin (33.4%) than the pregnancy rate to FTAI in cows treated with water (13.6%). The environmental condition (heat stress or not heat stress) did not affect the conclusion of effectiveness.

The effectiveness of gonadorelin for use with cloprostenol sodium to synchronize estrous cycles to allow for FTAI in beef cows was demonstrated in a field study at 10 different locations in the U.S. A total of 706 healthy, non-pregnant, primiparous or multiparous beef cows within 40-150 days postpartum were enrolled in the study. A total of 364 cows were administered gonadorelin (1 mL; 100 mcg gonadorelin as the acetate salt) and 342 cows were administered an equivalent volume of water for injection as an intramuscular injection twice in the following regimen:

Day 0: 100 mcg gonadorelin (as the acetate salt) or sterile water for injection

Day 7: 500 mcg cloprostenol (as cloprostenol sodium)

Day 9: 100 mcg gonadorelin (as the acetate salt) or sterile water for injection

Fixed time AI was performed immediately after the Day 9 injection. Cows were evaluated for pregnancy on Day 55 ± 5 days by trans-rectal ultrasound. Pregnancy rate to FTAI was significantly higher (P = 0.0006) in cows treated with gonadorelin (21.7%) than the pregnancy rate to FTAI in cows treated with water (7.4%).

The effectiveness of a 2-mL dose of CYSTORELIN delivering 100 mcg gonadorelin diacetate tetrahydrate (86 mcg gonadorelin) for use with cloprostenol sodium to synchronize estrous cycles to allow for FTAI in lactating dairy cows and beef cows was also demonstrated through references to scientific literature.

HOW SUPPLIED:

CYSTORELIN is available in a concentration of 50 mcg/mL gonadorelin diacetate tetrahydrate (43 mcg/mL gonadorelin) pH adjusted with potassium phosphate (monobasic and dibasic).

CYSTORELIN is supplied in multi-dose vials containing 10 mL, 30 mL, 50 mL, and 100 mL of sterile solution.

STORAGE, HANDLING, AND DISPOSAL:

Store at or below 77°F (25°C). Brief excursions to 86°F (30°C) are permitted. Use within 6 months of first puncture.

Principal Display Panel – 50 mL Bottle Carton

CYSTORELIN®
(gonadorelin)

(50 mcg/mL) gonadorelin diacetate tetrahydrate Injectable Solution

INDICATIONS FOR USE:

For the treatment of cystic ovaries in dairy cattle. For use with cloprostenol sodium to synchronize estrous cycles to allow for fixed-time artificial insemination (FTAI) in lactating dairy and beef cows.

CAUTION: Federal law restricts this drug to use by or on the order of a licensed veterinarian.

Approved by FDA under NADA # 098-379